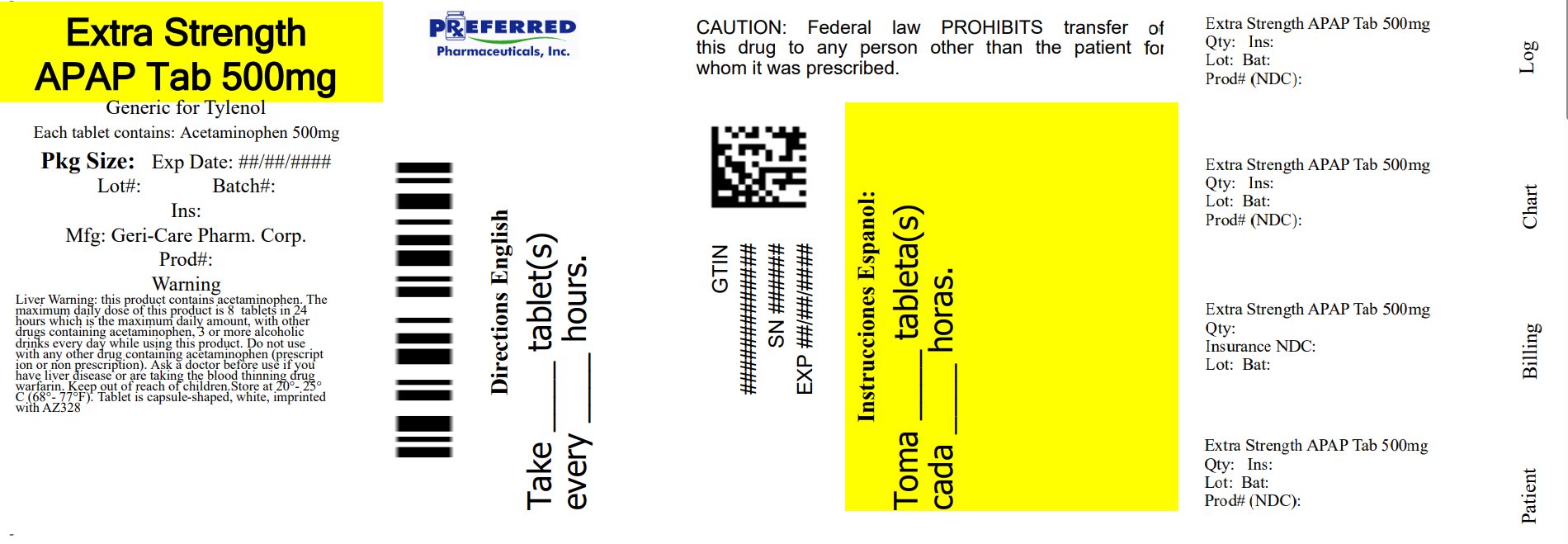 DRUG LABEL: Extra Strength Acetaminophen
NDC: 68788-4065 | Form: TABLET
Manufacturer: Preferred Pharmaceuticals Inc.
Category: otc | Type: HUMAN OTC DRUG LABEL
Date: 20260128

ACTIVE INGREDIENTS: ACETAMINOPHEN 500 mg/1 1
INACTIVE INGREDIENTS: POVIDONE, UNSPECIFIED; SODIUM STARCH GLYCOLATE TYPE A CORN; STARCH, CORN; STEARIC ACID

gc222

Active ingredient

Acetaminophen 500 mg

Purpose

Pain Reliever/Fever Reducer

Uses

- temporarily relieves minor aches and pains
- temporarily reduces fever

Warnings

Liver warning: This product contains acetaminophen.
Severe liver damage may occur if you take:

- more than 8 caplets (4,000 mg of acetaminophen) in 24 hours
- with other drugs containing acetaminophen
- 3 or more alcoholic drinks every day while using this product

Allergy alert: acetaminophen may cause severe skin reactions.
Symptoms may include:

- skin reddening
- blisters
- rash

If a skin reaction occurs, stop use and seek medical help right away.

Do not use

- with any other drug containing acetaminophen (prescription or nonprescription). If you are not sure whether a drug contains acetaminophen, ask a doctor or pharmacist.
- if you are allergic to acetaminophen or any of the inactive ingredients in this product

Ask a doctor before use if you have liver disease.

Ask a doctor or pharmacist before use if you are taking the blood thinning drug warfarin.

Stop use and ask a doctor if

- pain gets worse or lasts more than 10 days
- fever gets worse or lasts more than 3 days
- new symptom occur
- redness or swelling is present

These could be signs of a serious condition.
If pregnant or breast-feeding, ask a health professional before use.

Keep out of reach of children. In case of overdose, get medical
help or contact a Poison Control Center right away. Quick medical
attention is critical for adults as well as for children even if you
do not notice any signs or symptoms.

Directions

- do not take more than directed
- adults and children 12 years and over: take 2 caplets
  every 6 hours, as needed. Do not take more than 6
  caplets in 24 hours. Do not take for more than 10 days unless directed by a doctor.
- children under 12 years: ask a doctor

Other Information

- store at 20⁰C-25⁰C (68⁰F-77⁰F)
- Repackaged By: Preferred Pharmaceuticals Inc.

Inactive ingredients

corn starch, povidone, pregelatinized starch, sodium starch glycolate, stearic acid

Questions or comments?

1-800-540-3765